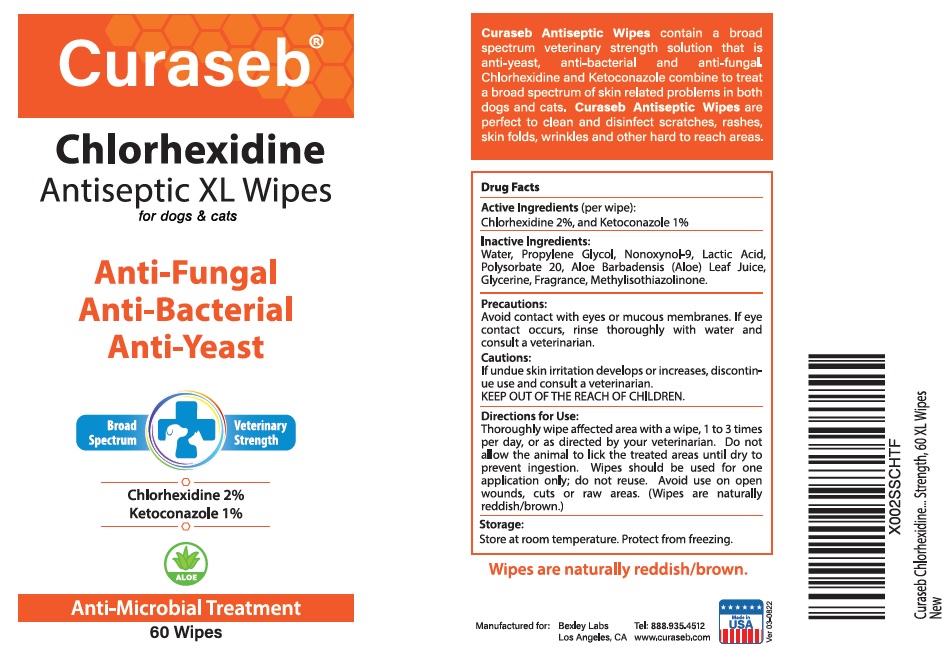 DRUG LABEL: Curaseb XL Wipes 60ct
NDC: 86133-105 | Form: CLOTH
Manufacturer: Bexley Labs
Category: animal | Type: OTC ANIMAL DRUG LABEL
Date: 20230224

ACTIVE INGREDIENTS: CHLORHEXIDINE GLUCONATE 2 g/100 mL; KETOCONAZOLE 1 g/100 mL
INACTIVE INGREDIENTS: WATER; PROPYLENE GLYCOL; NONOXYNOL-9; LACTIC ACID, UNSPECIFIED FORM; POLYSORBATE 20; ALOE VERA LEAF; GLYCERIN; METHYLISOTHIAZOLINONE

Curaseb® Chlorhexidine Antiseptic XL Wipes

Active Ingredients (per wipe):

Chlorhexidine 2%, and Ketoconazole 1%

Inactive Ingredients:

Water, Propylene Glycol, Nonoxynol-9, Lactic Acid, Polysorbate 20, Aloe Barbadensis (Aloe) Leaf Juice, Glycerin, Fragrance, Methylisothiazolinone.

Precautions:

Avoid contact with eyes or mucous membranes. If eye contact occurs, rinse thoroughly with water and consult a veterinarian.

Cautions:

If undue skin irritation develops or increases, discontinue use and consult a veterinarian.

KEEP OUT OF THE REACH OF CHILDREN.

Directions for Use:

Thoroughly wipe affected area with a wipe, 1 to 3 times per day, or as directed by your veterinarian. Do not allow the animal to lick the treated areas until dry to prevent ingestion. Wipes should be used for one application only; do not reuse. Avoid use on open wounds, cuts or raw areas. (Wipes are naturally reddish/brown.)

Storage:

Store at room temperature. Protect from freezing.

INDICATIONS AND USAGE

Curaseb Antiseptic Wipes contain a broad spectrum veterinary strength solution that is anti-yeast, anti-bacterial and anti-fungal. Chlorhexidine and Ketoconazole combine to treat a broad spectrum of skin related problems in both dogs and cats. Curaseb Antiseptic Wipes are perfect to clean and disinfect scratches, rashes, skin folds, wrinkles and other hard to reach areas.

for dogs & cats

Anti-Microbial Treatment

Manufactured for:
Bexley LabsLos Angeles, CA

Tel: 888.935.4512
www.curaseb.com

Made in USA